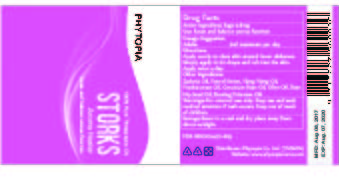 DRUG LABEL: Storks Synergy
NDC: 70470-1813 | Form: OIL
Manufacturer: PHYTOPIA CO., LTD.
Category: otc | Type: HUMAN OTC DRUG LABEL
Date: 20171001

ACTIVE INGREDIENTS: SAGE OIL 0.8 mg/50 mL
INACTIVE INGREDIENTS: FRANKINCENSE OIL; GERANIUM OIL, ALGERIAN TYPE; FENNEL OIL; CURCUMA ZANTHORRHIZA OIL; CANANGA OIL; OLIVE OIL; EVENING PRIMROSE OIL; ROSA RUBIGINOSA SEED OIL

Drug Facts

Sage 0.8mg

Use:

boost and balance uterus function

Dosage Suggestion

Adults 2ml maximum per day

Directions

Apply evenly to clean skin around lower abdomen. Simply apply 10~20 drops and rub into the skin. Apply twice a day.

Inactive Ingredients

Zadoria Oil, Fennel Sweet, Ylang Ylang Oil, Frankincense Oil, Geranium Rose Oil, Olive Oil, Rose Hip Seed Oil, Evening Primrose Oil.

Warnings

For external use only. Stop use and ask doctor if rash occurs. Keep out reach of children.

Other Information

Protect this product from excessive heat

and direct sun.

Warnings

For external use only. Stop use and ask doctor if rash occurs. Keep out reach of children.